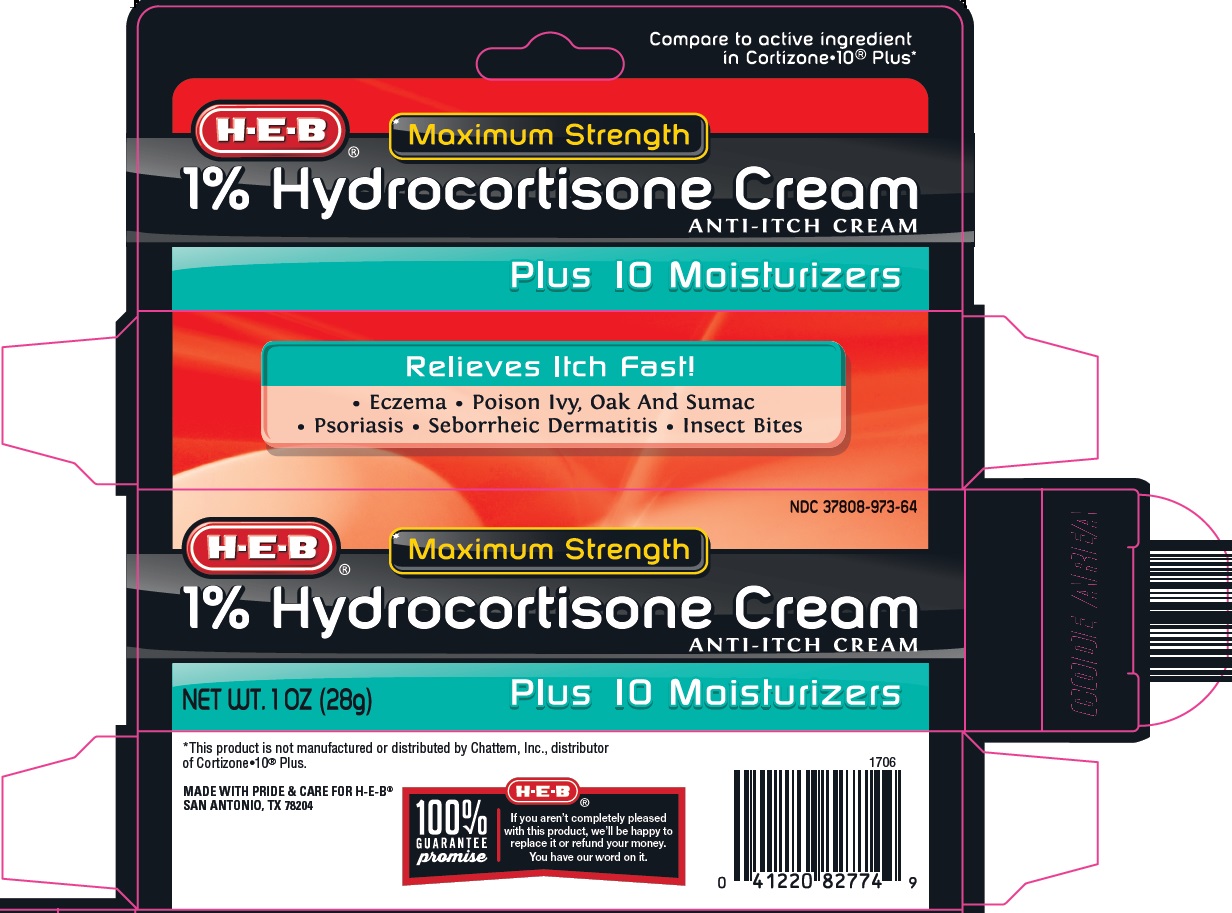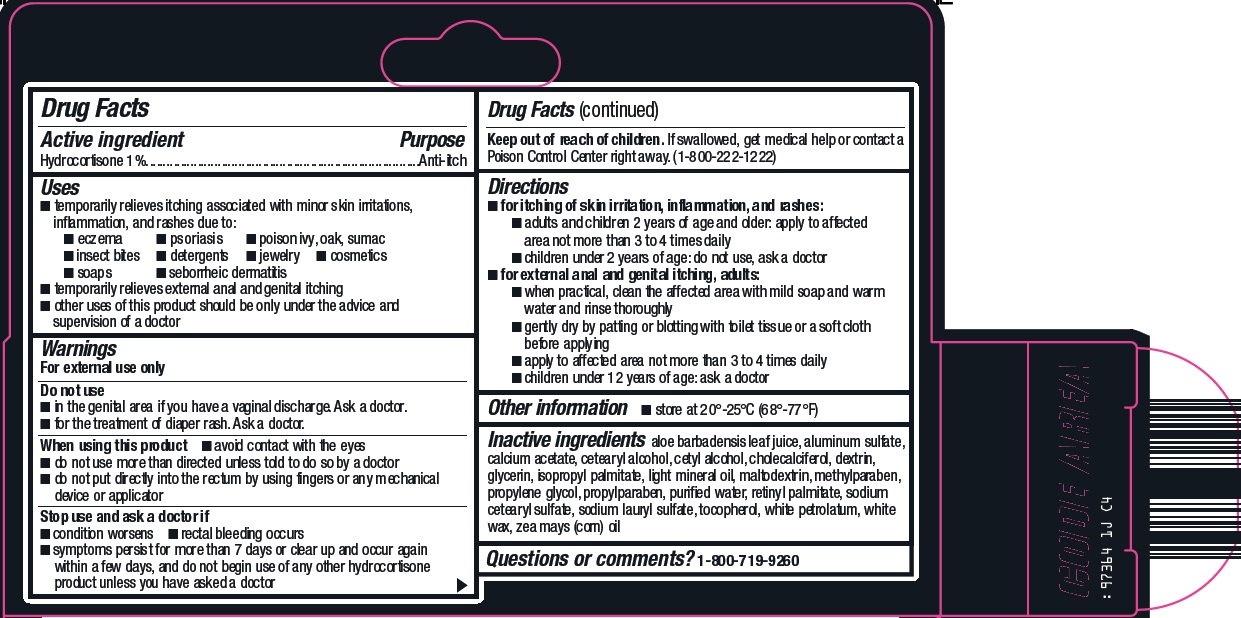 DRUG LABEL: hydrocortisone
NDC: 37808-973 | Form: CREAM
Manufacturer: H E B
Category: otc | Type: HUMAN OTC DRUG LABEL
Date: 20240929

ACTIVE INGREDIENTS: HYDROCORTISONE 1 g/100 g
INACTIVE INGREDIENTS: ALOE VERA LEAF; ALUMINUM SULFATE; CALCIUM ACETATE; CETOSTEARYL ALCOHOL; CETYL ALCOHOL; CHOLECALCIFEROL; GLYCERIN; ISOPROPYL PALMITATE; LIGHT MINERAL OIL; MALTODEXTRIN; METHYLPARABEN; PROPYLENE GLYCOL; PROPYLPARABEN; WATER; VITAMIN A PALMITATE; SODIUM CETOSTEARYL SULFATE; SODIUM LAURYL SULFATE; TOCOPHEROL; PETROLATUM; WHITE WAX; CORN OIL; ICODEXTRIN

HEB 1% Hydrocortisone Cream Drug Facts

Active ingredient

Hydrocortisone 1%

Purpose

Anti-itch

Uses

1. temporarily relieves itching associated with minor skin irritations, inflammation, and rashes due to:
2. eczema
3. psoriasis
4. poison ivy, oak, sumac
5. insect bites
6. detergents
7. jewelry
8. cosmetics
9. soaps
10. seborrheic dermatitis
11. temporarily relieves external anal and genital itching
12. other uses of this product should be only under the advice and supervision of a doctor

Warnings

For external use only

Do not use

1. in the genital area if you have a vaginal discharge. Ask a doctor.
2. for the treatment of diaper rash. Ask a doctor.

When using this product

1. avoid contact with the eyes
2. do not use more than directed unless told to do so by a doctor
3. do not put directly into the rectum by using fingers or any mechanical device or applicator

Stop use and ask a doctor if

1. condition worsens
2. symptoms persist for more than 7 days or clear up and occur again within a few days, and do not begin use of any other hydrocortisone product unless you have asked a doctor
3. rectal bleeding occurs

Keep out of reach of children.

If swallowed, get medical help or contact a Poison Control Center right away. (1-800-222-1222)

Directions

1. for itching of skin irritation, inflammation, and rashes:
2. adults and children 2 years of age and older: apply to affected area not more than 3 to 4 times daily
3. children under 2 years of age: do not use, ask a doctor
4. for external anal and genital itching, adults:
5. when practical, clean the affected area with mild soap and warm water and rinse thoroughly
6. gently dry by patting or blotting with toilet tissue or a soft cloth before applying
7. apply to affected area not more than 3 to 4 times daily
8. children under 12 years of age: ask a doctor

Other information

1. store at 20°-25°C (68°-77°F)

Inactive ingredients

aloe barbadensis leaf juice, aluminum sulfate, calcium acetate, cetearyl alcohol, cetyl alcohol, cholecalciferol, dextrin, glycerin, isopropyl palmitate, light mineral oil, maltodextrin, methylparaben, propylene glycol, propylparaben, purified water, retinyl palmitate, sodium cetearyl sulfate, sodium lauryl sulfate, tocopherol, white petrolatum, white wax, zea mays (corn) oil

Questions or comments?

1-800-719-9260

Principal Display Panel

Compare to active ingredient in Cortizone-10® Plus

Maximum Strength

1% Hydrocortisone Cream

ANTI-ITCH CREAM

Plus 10 Moisturizers

Maximum Strength

1% Hydrocortisone Cream

ANTI-ITCH CREAM

Plus 10 Moisturizers

NET WT. 1 OZ (28g)